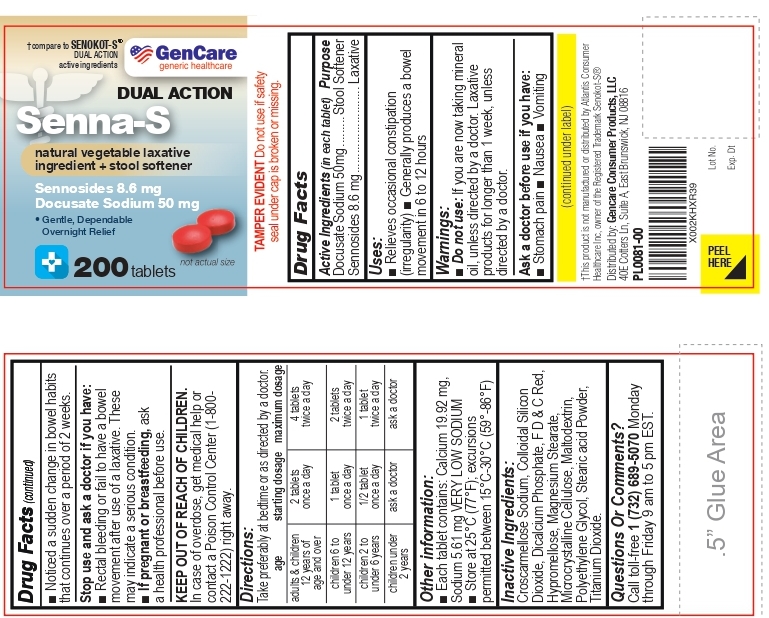 DRUG LABEL: Senna-S
NDC: 72090-030 | Form: TABLET
Manufacturer: Pioneer Life Sciences, LLC
Category: otc | Type: HUMAN OTC DRUG LABEL
Date: 20251229

ACTIVE INGREDIENTS: DOCUSATE SODIUM 50 mg/1 1; SENNOSIDES 8.6 mg/1 1
INACTIVE INGREDIENTS: Croscarmellose Sodium; Silicon Dioxide; ANHYDROUS DIBASIC CALCIUM PHOSPHATE; FD&C RED NO. 3; HYPROMELLOSE, UNSPECIFIED; Magnesium Stearate; Microcrystalline Cellulose; Maltodextrin; POLYETHYLENE GLYCOL, UNSPECIFIED; STEARIC ACID; Titanium Dioxide

Active Ingredients (in each tablet)

Docusate Sodium 50 mg

Sennosides 8.6 mg

Purpose

Stool softener

Laxative

Uses:

- Relieves occasional constipation (irregularity).
- Generally produces a bowel movement in 6 to 12 hours.

Warnings:

Do not use: If you are now taking mineral oil, unless directed by a doctor. Laxative products for longer than 1 week, unless directed by a doctor.

Ask a doctor before use if you have:

- Stomach pain
- nausea
- vomiting
- Noticed a sudden change in bowel habits that continues over a period of 2 weeks.

Stop use and ask a doctor if you have:

- Rectal bleeding or fail to have a bowel movement after use of a laxative. These may indicate a serious condition.

PREGNANCY OR BREAST FEEDING

- If pregnant or breast-feeding, ask a health professional before use.

Keep out of reach of children. In case of overdose, get medical help or contact a Poison Control Center (1-800-222-1222) right away.

DIRECTIONS

Take preferably at bedtime or as directed by a doctor.

age | starting dosage | maximum dosage
adults & children 12 years of age and over | 2 tablets once a day | 4 tablets twice a day
children 6 to under 12 years | 1 tablet once a day | 2 tablets twice a day
children 2 to under 6 years | 1 /2 tablet once a day | 1 tablet twice a day
children under 2 years | ask a doctor | ask a doctor

OTHER INFORMATION

- Each tablet contains: Calcium 19.92 mg, Sodium 5.61 mg VERY LOW SODIUM
- store at 25°C (77°F) excursions permitted between15°-30°C (59°-86°F)

INACTIVE INGREDIENTS

Croscarmellose Sodium, Colloidal Silicon Dioxide, Dicalcium Phosphate, F D & C Red, Hypromellose, Magnesium Stearate,
Microcrystalline Cellulose, Maltodextrin, Polyethylene Glycol, Stearic acid Powder, Titanium Dioxide.

QUESTIONS OR COMMENTS?

Call toll-free 1 (732) 689-5070 Monday through Friday 9 am to 5 pm EST.